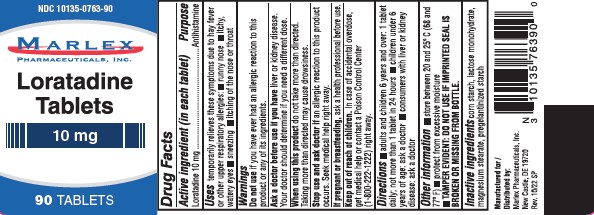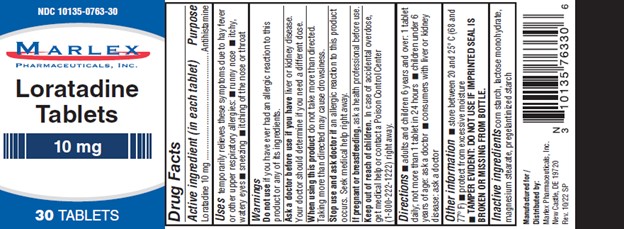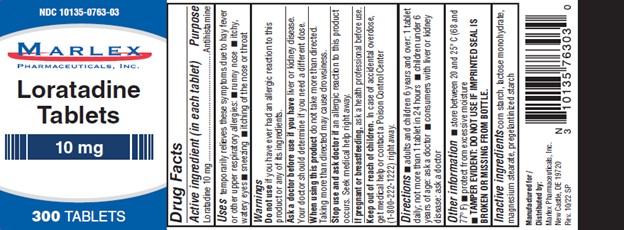 DRUG LABEL: Loratadine Allergy Relief
NDC: 10135-763 | Form: TABLET
Manufacturer: Marlex Pharmaceuticals, Inc.
Category: otc | Type: HUMAN OTC DRUG LABEL
Date: 20251118

ACTIVE INGREDIENTS: LORATADINE 10 mg/1 1
INACTIVE INGREDIENTS: LACTOSE MONOHYDRATE; MAGNESIUM STEARATE; STARCH, CORN

Loratadine Allergy Relief

Drug Facts

Active ingredient (in each tablet)

Loratadine, USP 10 mg

Purpose

Antihistamine

Uses

temporarily relieves these symptoms due to hay fever or other upper respiratory allergies:

- runny nose
- itchy, watery eyes
- sneezing
- itching of the nose or throat

Warnings

DO NOT USE

Do not useif you have ever had an allergic reaction to this product or any of its ingredients.

Ask a doctor before use if you haveliver or kidney disease. Your doctor should determine if you need a different dose.

WHEN USING

When using this productdo not take more than directed. Taking more than directed may cause drowsiness.

Stop use and ask a doctor ifan allergic reaction to this product occurs. Seek medical help right away.

PREGNANCY OR BREAST FEEDING

If pregnant or breast-feeding,ask a health professional before use.

Keep out of reach of children.In case of overdose, get medical help or contact a Poison Control Center right away (1-800-222-1222).

Directions

adults and children 6 years and over | 1 tablet daily; not more than 1 tablet in 24 hours
children under 6 years of age | ask a doctor
consumers with liver or kidney disease | ask a doctor

Other Information

- store between 20° to 25° C (68° to 77° F)
- protect from excessive moisture
- TAMPER EVIDENT: DO NOT USE IF IMPRINTED SEAL IS BROKEN OR MISSING FROM BOTTLE.

Inactive ingredients

corn starch, lactose monohydrate, magnesium stearate, pregelatinized starch

Manufactured for/ Distributed by:

Marlex Pharmaceuticals, Inc.

New Castle, DE 19720

Rev. 10/22 SP

PRINCIPAL DISPLAY PANEL

Loratadine 10mg Tablets

NDC 10135-0763-30

30 Tablets

Loratadine 10mg Tablets

NDC 10135-0763-90

90 Tablets

Loratadine 10mg Tablets

NDC 10135-0763-03

300 Tablets